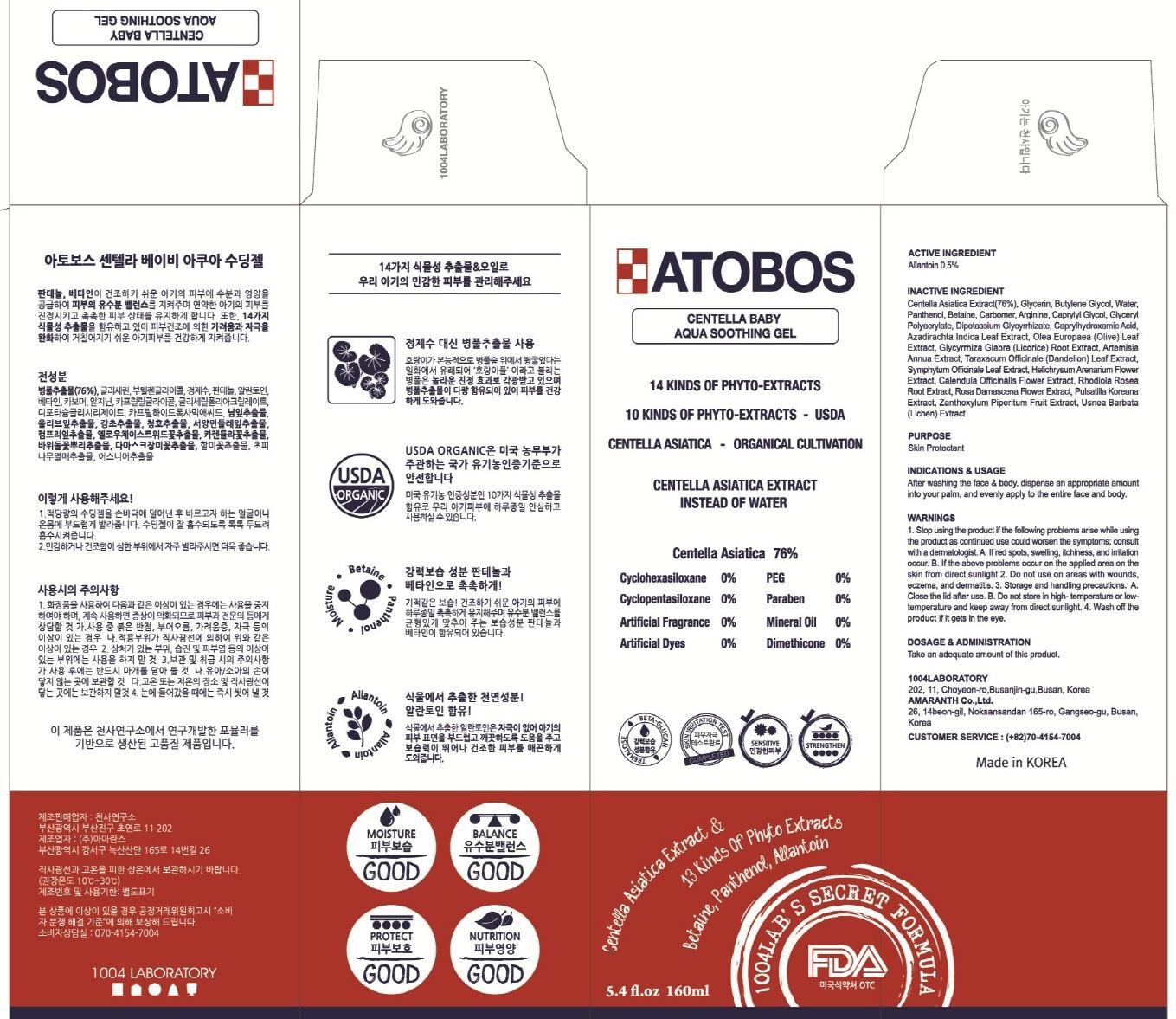 DRUG LABEL: ATOBOS CENTELLA BABY AQUA SOOTHING
NDC: 69739-100 | Form: GEL
Manufacturer: 1004LABORATORY
Category: otc | Type: HUMAN OTC DRUG LABEL
Date: 20150831

ACTIVE INGREDIENTS: Allantoin 0.8 mg/160 mL
INACTIVE INGREDIENTS: Centella Asiatica; Glycerin

ACTIVE INGREDIENT

Active Ingredient: Allantoin 0.5%

INACTIVE INGREDIENT

Inactive Ingredients: Centella Asiatica Extract, Glycerin, Butylene Glycol, Water, Panthenol, Betaine, Carbomer, Arginine, Caprylyl Glycol, Glyceryl Polyacrylate, Dipotassium Glycyrrhizate, Caprylhydroxamic Acid, Azadirachta Indica Leaf Extract, Olea Europaea (Olive) Leaf Extract, Glycyrrhiza Glabra (Licorice) Root Extract, Artemisia Annua Extract, Taraxacum Officinale (Dandelion) Leaf Extract, Symphytum Officinale Leaf Extract, Helichrysum Arenarium Flower Extract, Calendula Officinalis Flower Extract, Rhodiola Rosea Root Extract, Rosa Damascena Flower Extract, Pulsatilla Koreana Extract, Zanthoxylum Piperitum Fruit Extract, Usnea Barbata (Lichen) Extract

PURPOSE

Purpose: Skin Protectant

WARNINGS

Warnings: 1. Stop using the product if the following problems arise while using the product as continued use could worsen the symptoms; consult with a dermatologist. A. If red spots, swelling, itchiness, and irritation occur. B. If the above problems occur on the applied area on the skin from direct sunlight 2. Do not use on areas with wounds, eczema, and dermatitis. 3. Storage and handling precautions. A. Close the lid after use. B. Do not store in high- temperature or low- temperature and keep away from direct sunlight. 4. Wash off the product if it gets in the eye.

KEEP OUT OF REACH OF CHILDREN

INDICATIONS & USAGE

Indications & Usage: After washing the face & body, dispense an appropriate amount into your palm, and evenly apply to the entire face and body.

DOSAGE & ADMINISTRATION

Dosage & Administration: Take an adequate amount of this product.